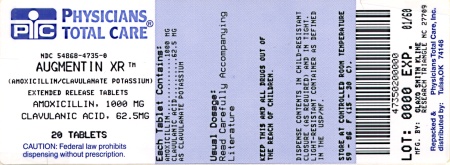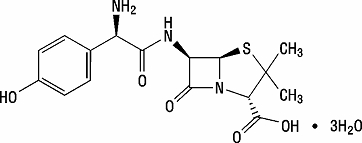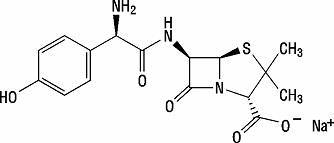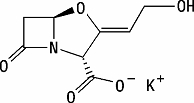 DRUG LABEL: AugmentinXR
NDC: 54868-4735 | Form: TABLET, FILM COATED, EXTENDED RELEASE
Manufacturer: Physicians Total Care, Inc.
Category: prescription | Type: HUMAN PRESCRIPTION DRUG LABEL
Date: 20101122

ACTIVE INGREDIENTS: AMOXICILLIN 1000 mg/1 1; CLAVULANATE POTASSIUM 62.5 mg/1 1
INACTIVE INGREDIENTS: CITRIC ACID MONOHYDRATE; SILICON DIOXIDE; HYPROMELLOSES; MAGNESIUM STEARATE; CELLULOSE, MICROCRYSTALLINE; POLYETHYLENE GLYCOL; SODIUM STARCH GLYCOLATE TYPE A POTATO; TITANIUM DIOXIDE; XANTHAN GUM

To reduce the development of drug-resistant bacteria and maintain the effectiveness of AUGMENTIN XR (amoxicillin/clavulanate potassium) and other antibacterial drugs, AUGMENTIN XR should be used only to treat or prevent infections that are proven or strongly suspected to be caused by bacteria.

DESCRIPTION

AUGMENTIN XR is an oral antibacterial combination consisting of the semisynthetic antibiotic amoxicillin (present as amoxicillin trihydrate and amoxicillin sodium) and the β-lactamase inhibitor clavulanate potassium (the potassium salt of clavulanic acid). Amoxicillin is an analog of ampicillin, derived from the basic penicillin nucleus 6-aminopenicillanic acid. The amoxicillin trihydrate molecular formula is C16H19N3O5S•3H2O, and the molecular weight is 419.45. Chemically, amoxicillin trihydrate is (2S,5R ,6R)-6-[(R)-(-)-2-Amino-2-(p-hydroxyphenyl)acetamido]-3,3-dimethyl-7-oxo-4-thia-1-azabicyclo[3.2.0]heptane-2-carboxylic acid trihydrate and may be represented structurally as:

The amoxicillin sodium molecular formula is C16H18N3NaO5S, and the molecular weight is 387.39. Chemically, amoxicillin sodium is [2S-[2α,5α,6β(S *)]]-6-[[Amino(4-hydroxyphenyl)acetyl]amino]-3,3-dimethyl-7-oxo-4-thia-1-azabicyclo[3.2.0]heptane-2-carboxylic acid monosodium salt and may be represented structurally as:

Clavulanic acid is produced by the fermentation of Streptomyces clavuligerus. It is a β-lactam structurally related to the penicillins and possesses the ability to inactivate a wide variety of β-lactamases by blocking the active sites of these enzymes. Clavulanic acid is particularly active against the clinically important plasmid-mediated β-lactamases frequently responsible for transferred drug resistance to penicillins and cephalosporins. The clavulanate potassium molecular formula is C8H8KNO5, and the molecular weight is 237.25. Chemically, clavulanate potassium is potassium (Z)-(2R ,5R)-3-(2-hydroxyethylidene)-7-oxo-4-oxa-1-azabicyclo[3.2.0]-heptane-2-carboxylate, and may be represented structurally as:

Inactive Ingredients

Citric acid, colloidal silicon dioxide, hypromellose, magnesium stearate, microcrystalline cellulose, polyethylene glycol, sodium starch glycolate, titanium dioxide, and xanthan gum.

Each tablet of AUGMENTIN XR contains 12.6 mg (0.32 mEq) of potassium and 29.3 mg (1.27 mEq) of sodium.

CLINICAL PHARMACOLOGY

Amoxicillin and clavulanate potassium are well absorbed from the gastrointestinal tract after oral administration of AUGMENTIN XR.

AUGMENTIN XR is an extended-release formulation which provides sustained plasma concentrations of amoxicillin. Amoxicillin systemic exposure achieved with AUGMENTIN XR is similar to that produced by the oral administration of equivalent doses of amoxicillin alone. In a study of healthy adult volunteers, the pharmacokinetics of AUGMENTIN XR were compared when administered in a fasted state, at the start of a standardized meal (612 kcal, 89.3 g carb, 24.9 g fat, and 14.0 g protein), or 30 minutes after a high-fat meal. When the systemic exposure to both amoxicillin and clavulanate is taken into consideration, AUGMENTIN XR is optimally administered at the start of a standardized meal. Absorption of amoxicillin is decreased in the fasted state. AUGMENTIN XR is not recommended to be taken with a high-fat meal, because clavulanate absorption is decreased. The pharmacokinetics of the components of AUGMENTIN XR following administration of two AUGMENTIN XR tablets at the start of a standardized meal are presented in Table 1.

Table 1. Mean (SD) Pharmacokinetic Parameters for Amoxicillin and Clavulanate Following Oral Administration of Two AUGMENTIN XR Tablets (2,000 mg/125 mg) to Healthy Adult Volunteers (n = 55) Fed a Standardized Meal
Parameter (units) | Amoxicillin | Clavulanate
AUC(0-inf) (mcg•hr/mL) | 71.6 (16.5) | 5.29 (1.55)
Cmax (mcg/mL) | 17.0 (4.0) | 2.05 (0.80)
Tmax (hours)a | 1.50 (1.00 - 6.00) | 1.03 (0.75 - 3.00)
T½ (hours) | 1.27 (0.20) | 1.03 (0.17)

a Median (range).

The half-life of amoxicillin after the oral administration of AUGMENTIN XR is approximately 1.3 hours, and that of clavulanate is approximately 1.0 hour.

Clearance of amoxicillin is predominantly renal, with approximately 60% to 80% of the dose being excreted unchanged in urine, whereas clearance of clavulanate has both a renal (30% to 50%) and a non-renal component.

Concurrent administration of probenecid delays amoxicillin excretion but does not delay renal excretion of clavulanate.

In a study of adults, the pharmacokinetics of amoxicillin and clavulanate were not affected by administration of an antacid (MAALOX®), either simultaneously with or 2 hours after AUGMENTIN XR.

Neither component in AUGMENTIN XR is highly protein-bound; clavulanate has been found to be approximately 25% bound to human serum and amoxicillin approximately 18% bound.

Amoxicillin diffuses readily into most body tissues and fluids, with the exception of the brain and spinal fluid. The results of experiments involving the administration of clavulanic acid to animals suggest that this compound, like amoxicillin, is well distributed in body tissues.

In a study of pediatric patients with acute bacterial sinusitis, 7 to 15 years of age, and weighing at least 40 kg, the pharmacokinetics of amoxicillin and clavulanate were assessed following administration of AUGMENTIN XR 2000 mg/125 mg (as two 1000 mg/62.5 mg tablets) every 12 hours with food (Table 2).

Table 2. Mean (SD) Pharmacokinetic Parameters for Amoxicillin and Clavulanate Following Oral Administration of Two AUGMENTIN XR Tablets (2,000 mg/125 mg) Every 12 Hours With Food to Pediatric Patients (7 to 15 Years of Age and Weighing ≥ 40kg) With Acute Bacterial Sinusitis
Parameter (units) | Amoxicillin; (n=24) | Clavulanate; (n=23)
AUC(0-τ) (mcg•hr/mL) | 57.8 (15.6) | 3.18 (1.37)
Cmax (mcg/mL) | 11.0 (3.34) | 1.17 (0.67)
Tmax (hours)a | 2.0 (1.0 – 5.0) | 2.0 (1.0 – 4.0)
T½ (hours) | 3.32 (2.21)b | 0.94 (0.13)c

a Median (range).

b n=18.

c n=17.

Microbiology

Amoxicillin is a semisynthetic antibiotic with a broad spectrum of bactericidal activity against many gram-positive and gram-negative microorganisms. Amoxicillin is, however, susceptible to degradation by β-lactamases, and therefore, its spectrum of activity does not include organisms which produce these enzymes. Clavulanic acid is a β-lactam, structurally related to penicillin, which possesses the ability to inactivate a wide range of β-lactamase enzymes commonly found in microorganisms resistant to penicillins and cephalosporins. In particular, it has good activity against the clinically important plasmid-mediated β-lactamases frequently found responsible for transferred drug resistance.

The clavulanic acid component of AUGMENTIN XR protects amoxicillin from degradation by β-lactamase enzymes and effectively extends the antibiotic spectrum of amoxicillin to include many bacteria normally resistant to amoxicillin and other β-lactam antibiotics.

Amoxicillin/clavulanic acid has been shown to be active against most isolates of the following microorganisms, both in vitro and in clinical infections as described in the INDICATIONS AND USAGE section.

Aerobic Gram-Positive Microorganisms

Streptococcus pneumoniae (including isolates with penicillin MICs ≤ 2 mcg/mL)

Staphylococcus aureus (including β-lactamase−producing isolates)

NOTE: Staphylococci which are resistant to methicillin/oxacillin must be considered resistant to amoxicillin/clavulanic acid.

Aerobic Gram-Negative Microorganisms

Haemophilus influenzae (including β-lactamase−producing isolates)

Moraxella catarrhalis (including β-lactamase−producing isolates)

Haemophilus parainfluenzae (including β-lactamase−producing isolates)

Klebsiella pneumoniae (all known isolates are β-lactamase−producing)

The following in vitro data are available, but their clinical significance is unknown.

At least 90% of the following microorganisms exhibit in vitro minimum inhibitory concentrations (MICs) less than or equal to the susceptible breakpoint for amoxicillin/clavulanic acid.^1,2 However, the safety and efficacy of amoxicillin/clavulanic acid in treating infections due to these microorganisms have not been established in adequate and well-controlled trials.

Aerobic Gram-Positive Microorganisms

Streptococcus pyogenes

Anaerobic Microorganisms

Bacteroides fragilis (including β-lactamase−producing isolates)

Fusobacterium nucleatum (including β-lactamase−producing isolates)

Peptostreptococcus magnus

Peptostreptococcus micros

NOTE: S. pyogenes, P. magnus, and P. micros do not produce β-lactamase, and therefore, are susceptible to amoxicillin alone. Adequate and well-controlled clinical trials have established the effectiveness of amoxicillin alone in treating certain clinical infections due to S. pyogenes.

Susceptibility Test Methods

When available, the clinical microbiology laboratory should provide cumulative results of in vitro susceptibility test results for antimicrobial drugs used in local hospitals and practice areas to the physician as periodic reports that describe the susceptibility profile of nosocomial and community-acquired pathogens. These reports should aid the physician in selecting the most effective antimicrobial.

Dilution Technique

Quantitative methods are used to determine antimicrobial minimum inhibitory concentrations (MICs). These MICs provide estimates of the susceptibility of bacteria to antimicrobial compounds. The MICs should be determined using a standardized procedure.^1,3 Standardized procedures are based on dilution methods (broth or agar; broth for S. pneumoniae and H. influenzae) or equivalent with standardized inoculum concentration and standardized concentrations of amoxicillin/clavulanate potassium powder.

The recommended dilution pattern utilizes a constant amoxicillin/clavulanate potassium ratio of 2 to 1 in all tubes with varying amounts of amoxicillin. MICs are expressed in terms of the amoxicillin concentration in the presence of clavulanic acid at a constant 2 parts amoxicillin to 1 part clavulanic acid. The MIC values should be interpreted according to criteria provided in Table 3.

Diffusion Technique

Quantitative methods that require measurement of zone diameters also provide reproducible estimates of the susceptibility of bacteria to antimicrobials. One such standardized technique requires the use of a standardized inoculum concentration.^1,4 This procedure uses paper disks impregnated with 30 mcg amoxicillin/clavulanate potassium (20 mcg amoxicillin plus 10 mcg clavulanate potassium) to test susceptibility of microorganisms to amoxicillin/clavulanate potassium. Disk diffusion zone sizes should be interpreted according to criteria provided in Table 3.

Table 3. Susceptibility Test Result Interpretive Criteria for Amoxicillin/Clavulanate Potassium
 | Minimum Inhibitory Concentration; (mcg/mL) | Disk Diffusion; (Zone Diameter in mm)
Pathogen | S | I | R | S | I | R
Haemophilus spp. | ≤ 4/2 | Not applicable (NA) | ≥ 8/4 | ≥ 20 | NA | ≤ 19
Klebsiella pneumoniae | ≤ 8/4 | 16/8 | ≥ 32/16 | ≥ 18 | 14 to 17 | ≤ 13
Staphylococcus spp. | ≤ 4/2 | NA | ≥ 8/4 | ≥ 20 | NA | ≤ 19
Streptococcus pneumoniae | ≤ 2/1 | 4/2 | ≥ 8/4 | NA

NOTE: Susceptibility of S. pneumoniae should be determined using a 1-mcg oxacillin disk. Isolates with oxacillin zone sizes of ≥ 20 mm are susceptible to amoxicillin/clavulanate acid. An amoxicillin/clavulanate acid MIC should be determined on isolates of S. pneumoniae with oxacillin zone sizes of ≤ 19 mm.

NOTE: β-lactamase−negative, ampicillin-resistant H. influenzae isolates must be considered resistant to amoxicillin/clavulanic acid.

A report of S (“Susceptible”) indicates that the antimicrobial is likely to inhibit growth of the pathogen if the antimicrobial compound in the blood reaches the concentration usually achievable. A report of I (“Intermediate”) indicates that the result should be considered equivocal, and, if the microorganism is not fully susceptible to alternative, clinically feasible antimicrobials, the test should be repeated. This category implies possible clinical applicability in body sites where the drug is physiologically concentrated or in situations where high doses of antimicrobial can be used. This category also provides a buffer zone that prevents small uncontrolled technical factors from causing major discrepancies in interpretation. A report of R (“Resistant”) indicates that the antimicrobial is not likely to inhibit growth of the pathogen if the antimicrobial compound in the blood reaches the concentration usually achievable; other therapy should be selected.

Standardized susceptibility test procedures require the use of quality control microorganisms to determine the performance of the test procedures.^1,3,4 Standard amoxicillin/clavulanate potassium powder should provide the MIC ranges for the quality control organisms in Table 4. For the disk diffusion technique, the 30 mcg amoxicillin/clavulanate potassium disk should provide the zone diameter ranges for the quality control organisms in Table 4.

Table 4. Acceptable Quality Control Ranges for Amoxicillin/Clavulanate Potassium
Quality Control Organism | Minimum Inhibitory Concentration Range (mcg/mL) | Disk Diffusion; (Zone Diameter Range in mm)
Escherichia coli ATCC®a 35218b; (H. influenzae quality control) | 4/2 to 16/8 | 17 to 22
Escherichia coli ATCC 25922 | 2/1 to 8/4 | 18 to 24
Haemophilus influenzae ATCC 49247 | 2/1 to 16/8 | 15 to 23
Staphylococcus aureus ATCC 29213 | 0.12/0.06 to 0.5/0.25 | Not applicable (NA)
Staphylococcus aureus ATCC 25923 | NA | 28 to 36
Streptococcus pneumoniae ATCC 49619 | 0.03/0.015 to 0.12/0.06 | NA

a ATCC is a trademark of the American Type Culture Collection.

b When using Haemophilus Test Medium (HTM).

INDICATIONS AND USAGE

AUGMENTIN XR Extended Release Tablets are indicated for the treatment of patients with community-acquired pneumonia or acute bacterial sinusitis due to confirmed, or suspected β-lactamase−producing pathogens (i.e., H. influenzae, M. catarrhalis, H. parainfluenzae, K. pneumoniae, or methicillin-susceptible S. aureus) and S. pneumoniae with reduced susceptibility to penicillin (i.e., penicillin MICs = 2 mcg/mL). AUGMENTIN XR is not indicated for the treatment of infections due to S. pneumoniae with penicillin MICs ≥ 4 mcg/mL. Data are limited with regard to infections due to S. pneumoniaewith penicillin MICs ≥ 4 mcg/mL (see CLINICAL STUDIES).

Of the common epidemiological risk factors for patients with resistant pneumococcal infections, only age > 65 years was studied. Patients with other common risk factors for resistant pneumococcal infections (e.g., alcoholism, immune-suppressive illness, and presence of multiple co-morbid conditions) were not studied.

In patients with community-acquired pneumonia in whom penicillin-resistant S. pneumoniae is suspected, bacteriological studies should be performed to determine the causative organisms and their susceptibility when AUGMENTIN XR is prescribed.

Acute bacterial sinusitis or community-acquired pneumonia due to a penicillin-susceptible strain of S. pneumoniae plus a β-lactamase−producing pathogen can be treated with another AUGMENTIN® (amoxicillin/clavulanate potassium) product containing lower daily doses of amoxicillin (i.e., 500 mg every 8 hours or 875 mg every 12 hours). Acute bacterial sinusitis or community-acquired pneumonia due to S. pneumoniae alone can be treated with amoxicillin.

To reduce the development of drug-resistant bacteria and maintain the effectiveness of AUGMENTIN XR and other antibacterial drugs, AUGMENTIN XR should be used only to treat or prevent infections that are proven or strongly suspected to be caused by susceptible bacteria. When culture and susceptibility information are available, they should be considered in selecting or modifying antibacterial therapy. In the absence of such data, local epidemiology and susceptibility patterns may contribute to the empiric selection of therapy.

CONTRAINDICATIONS

AUGMENTIN XR is contraindicated in patients with a history of allergic reactions to any penicillin. It is also contraindicated in patients with a previous history of cholestatic jaundice/hepatic dysfunction associated with treatment with amoxicillin/clavulanate potassium.

AUGMENTIN XR is contraindicated in patients with severe renal impairment (creatinine clearance < 30 mL/min.) and in hemodialysis patients.

WARNINGS

SERIOUS AND OCCASIONALLY FATAL HYPERSENSITIVITY (ANAPHYLACTIC) REACTIONS HAVE BEEN REPORTED IN PATIENTS ON PENICILLIN THERAPY. THESE REACTIONS ARE MORE LIKELY TO OCCUR IN INDIVIDUALS WITH A HISTORY OF PENICILLIN HYPERSENSITIVITY AND/OR A HISTORY OF SENSITIVITY TO MULTIPLE ALLERGENS. THERE HAVE BEEN REPORTS OF INDIVIDUALS WITH A HISTORY OF PENICILLIN HYPERSENSITIVITY WHO HAVE EXPERIENCED SEVERE REACTIONS WHEN TREATED WITH CEPHALOSPORINS. BEFORE INITIATING THERAPY WITH AUGMENTIN XR, CAREFUL INQUIRY SHOULD BE MADE CONCERNING PREVIOUS HYPERSENSITIVITY REACTIONS TO PENICILLINS, CEPHALOSPORINS, OR OTHER ALLERGENS. IF AN ALLERGIC REACTION OCCURS, AUGMENTIN XR SHOULD BE DISCONTINUED AND THE APPROPRIATE THERAPY INSTITUTED. SERIOUS ANAPHYLACTIC REACTIONS REQUIRE IMMEDIATE EMERGENCY TREATMENT WITH EPINEPHRINE. OXYGEN, INTRAVENOUS STEROIDS, AND AIRWAY MANAGEMENT, INCLUDING INTUBATION, SHOULD ALSO BE ADMINISTERED AS INDICATED.

Clostridium difficile associated diarrhea (CDAD) has been reported with use of nearly all antibacterial agents, including AUGMENTIN XR, and may range in severity from mild diarrhea to fatal colitis. Treatment with antibacterial agents alters the normal flora of the colon leading to overgrowth of C. difficile.

C. difficile produces toxins A and B which contribute to the development of CDAD. Hypertoxin producing strains of C. difficile cause increased morbidity and mortality, as these infections can be refractory to antimicrobial therapy and may require colectomy. CDAD must be considered in all patients who present with diarrhea following antibiotic use. Careful medical history is necessary since CDAD has been reported to occur over two months after the administration of antibacterial agents.

If CDAD is suspected or confirmed, ongoing antibiotic use not directed against C. difficile may need to be discontinued. Appropriate fluid and electrolyte management, protein supplementation, antibiotic treatment of C. difficile, and surgical evaluation should be instituted as clinically indicated.

AUGMENTIN XR should be used with caution in patients with evidence of hepatic dysfunction. Hepatic toxicity associated with the use of amoxicillin/clavulanate potassium is usually reversible. On rare occasions, deaths have been reported (less than 1 death reported per estimated 4 million prescriptions worldwide). These have generally been cases associated with serious underlying diseases or concomitant medications (see CONTRAINDICATIONS and ADVERSE REACTIONS—Liver).

PRECAUTIONS

General

While amoxicillin/clavulanate potassium possesses the characteristic low toxicity of the penicillin group of antibiotics, periodic assessment of organ system functions, including renal, hepatic, and hematopoietic function, is advisable if therapy is for longer than the drug is approved for administration.

A high percentage of patients with mononucleosis who receive ampicillin develop an erythematous skin rash. Thus, ampicillin-class antibiotics should not be administered to patients with mononucleosis.

The possibility of superinfections with mycotic or bacterial pathogens should be kept in mind during therapy. If superinfections occur (usually involving Pseudomonas spp. or Candida spp.), the drug should be discontinued and/or appropriate therapy instituted.

Prescribing AUGMENTIN XR in the absence of a proven or strongly suspected bacterial infection or a prophylactic indication is unlikely to provide benefit to the patient and increases the risk of the development of drug-resistant bacteria.

Information for Patients

AUGMENTIN XR should be taken every 12 hours with a meal or snack to reduce the possibility of gastrointestinal upset. If diarrhea develops and is severe or lasts more than 2 or 3 days, call your doctor.

Diarrhea is a common problem caused by antibiotics which usually ends when the antibiotic is discontinued. Sometimes after starting treatment with antibiotics, patients can develop watery and bloody stools (with or without stomach cramps and fever) even as late as 2 or more months after having taken the last dose of the antibiotic. If this occurs, patients should contact their physician as soon as possible.

Patients should be counseled that antibacterial drugs, including AUGMENTIN XR, should only be used to treat bacterial infections. They do not treat viral infections (e.g., the common cold). When AUGMENTIN XR is prescribed to treat a bacterial infection, patients should be told that although it is common to feel better early in the course of therapy, the medication should be taken exactly as directed. Skipping doses or not completing the full course of therapy may: (1) decrease the effectiveness of the immediate treatment, and (2) increase the likelihood that bacteria will develop resistance and will not be treatable by AUGMENTIN XR or other antibacterial drugs in the future. Discard any unused medicine.

Drug Interactions

Probenecid decreases the renal tubular secretion of amoxicillin. Concurrent use with AUGMENTIN XR may result in increased and prolonged blood levels of amoxicillin. Coadministration of probenecid cannot be recommended.

Abnormal prolongation of prothrombin time (increased international normalized ratio [INR]) has been reported rarely in patients receiving amoxicillin and oral anticoagulants. Appropriate monitoring should be undertaken when anticoagulants are prescribed concurrently. Adjustments in the dose of oral anticoagulants may be necessary to maintain the desired level of anticoagulation.

The concurrent administration of allopurinol and ampicillin increases substantially the incidence of rashes in patients receiving both drugs as compared to patients receiving ampicillin alone. It is not known whether this potentiation of ampicillin rashes is due to allopurinol or the hyperuricemia present in these patients. In controlled clinical trials of AUGMENTIN XR, 25 patients received concomitant allopurinol and AUGMENTIN XR. No rashes were reported in these patients. However, this sample size is too small to allow for any conclusions to be drawn regarding the risk of rashes with concomitant AUGMENTIN XR and allopurinol use.

In common with other broad-spectrum antibiotics, AUGMENTIN XR may reduce the efficacy of oral contraceptives.

Drug/Laboratory Test Interactions

Oral administration of AUGMENTIN XR will result in high urine concentrations of amoxicillin. High urine concentrations of ampicillin may result in false-positive reactions when testing for the presence of glucose in urine using CLINITEST®, Benedict’s Solution, or Fehling’s Solution. Since this effect may also occur with amoxicillin and therefore AUGMENTIN XR, it is recommended that glucose tests based on enzymatic glucose oxidase reactions (such as CLINISTIX®) be used.

Following administration of ampicillin to pregnant women, a transient decrease in plasma concentration of total conjugated estriol, estriol-glucuronide, conjugated estrone, and estradiol has been noted. This effect may also occur with amoxicillin, and therefore, AUGMENTIN XR.

Carcinogenesis, Mutagenesis, Impairment of Fertility

Long-term studies in animals have not been performed to evaluate carcinogenic potential. The mutagenic potential of AUGMENTIN was investigated in vitro with an Ames test, a human lymphocyte cytogenetic assay, a yeast test, and a mouse lymphoma forward mutation assay, and in vivo with mouse micronucleus tests and a dominant lethal test. All were negative apart from the in vitro mouse lymphoma assay, where weak activity was found at very high, cytotoxic concentrations. AUGMENTIN at oral doses of up to 1,200 mg/kg/day (1.9 times the maximum human dose of amoxicillin and 15 times the maximum human dose of clavulanate based on body surface area) was found to have no effect on fertility and reproductive performance in rats dosed with a 2:1 ratio formulation of amoxicillin:clavulanate.

Pregnancy Teratogenic Effects

Pregnancy Category B. Reproduction studies performed in pregnant rats and mice given AUGMENTIN at oral doses up to 1,200 mg/kg/day revealed no evidence of harm to the fetus due to AUGMENTIN. In terms of body surface area, the doses in rats were 1.6 times the maximum human oral dose of amoxicillin and 13 times the maximum human dose for clavulanate. For mice, these doses were 0.9 and 7.4 times the maximum human oral dose of amoxicillin and clavulanate, respectively. There are, however, no adequate and well-controlled studies in pregnant women. Because animal reproduction studies are not always predictive of human response, this drug should be used during pregnancy only if clearly needed.

Labor and Delivery

Oral ampicillin-class antibiotics are generally poorly absorbed during labor. Studies in guinea pigs have shown that intravenous administration of ampicillin decreased the uterine tone, frequency of contractions, height of contractions, and duration of contractions. However, it is not known whether the use of AUGMENTIN XR in humans during labor or delivery has immediate or delayed adverse effects on the fetus, prolongs the duration of labor, or increases the likelihood that forceps delivery or other obstetrical intervention or resuscitation of the newborn will be necessary. In a single study in women with premature rupture of fetal membranes, it was reported that prophylactic treatment with AUGMENTIN may be associated with an increased risk of necrotizing enterocolitis in neonates.

Nursing Mothers

Ampicillin-class antibiotics are excreted in the milk; therefore, caution should be exercised when AUGMENTIN XR is administered to a nursing woman.

Pediatric Use

The safety and effectiveness of AUGMENTIN XR have been established for pediatric patients weighing ≥ 40 kg who are able to swallow tablets. Use of AUGMENTIN XR in these pediatric patients is supported by evidence from adequate and well-controlled trials of adults with acute bacterial sinusitis and community-acquired pneumonia with additional data from a pediatric pharmacokinetic study.

A pharmacokinetic study in pediatric patients (7 to 15 years of age and weighing ≥ 40 kg) was conducted (see CLINICAL PHARMACOLOGY).

The adverse event profile in 44 pediatric patients who received at least one dose of AUGMENTIN XR was consistent with the established adverse event profile for the product in adults.

Geriatric Use

Of the total number of subjects in clinical studies of AUGMENTIN XR, 18.4% were 65 years or older and 7.2% were 75 years or older. No overall differences in safety and effectiveness were observed between these subjects and younger subjects, and other clinical experience has not reported differences in responses between the elderly and younger patients, but a greater sensitivity of some older individuals cannot be ruled out.

This drug is known to be substantially excreted by the kidney, and the risk of dose-dependent toxic reactions to this drug may be greater in patients with impaired renal function. Because elderly patients are more likely to have decreased renal function, it may be useful to monitor renal function.

Each tablet of AUGMENTIN XR contains 29.3 mg (1.27 mEq) of sodium.

ADVERSE REACTIONS

In clinical trials, 5,643 patients have been treated with AUGMENTIN XR. The majority of side effects observed in clinical trials were of a mild and transient nature; 2% of patients discontinued therapy because of drug-related side effects. The most frequently reported adverse effects which were suspected or probably drug-related were diarrhea (14.5%), vaginal mycosis (3.3%) nausea (2.1%), and loose stools (1.6%). AUGMENTIN XR had a higher rate of diarrhea which required corrective therapy (3.8% versus 2.6% for AUGMENTIN XR and all comparators, respectively).

The following adverse reactions have been reported for ampicillin-class antibiotics:

Gastrointestinal

Diarrhea, nausea, vomiting, indigestion, gastritis, stomatitis, glossitis, black “hairy” tongue, mucocutaneous candidiasis, enterocolitis, and hemorrhagic/pseudomembranous colitis. Onset of pseudomembranous colitis symptoms may occur during or after antibiotic treatment (see WARNINGS).

Hypersensitivity Reactions

Skin rashes, pruritus, urticaria, angioedema, serum sickness-like reactions (urticaria or skin rash accompanied by arthritis, arthralgia, myalgia, and frequently fever), erythema multiforme (rarely Stevens-Johnson syndrome), acute generalized exanthematous pustulosis, hypersensitivity vasculitis, and an occasional case of exfoliative dermatitis (including toxic epidermal necrolysis) have been reported. Whenever such reactions occur, the drug should be discontinued, unless the opinion of the physician dictates otherwise. Serious and occasional fatal hypersensitivity (anaphylactic) reactions can occur with oral penicillin (see WARNINGS).

Liver

A moderate rise in AST (SGOT) and/or ALT (SGPT) has been noted in patients treated with ampicillin-class antibiotics, but the significance of these findings is unknown. Hepatic dysfunction, including hepatitis and cholestatic jaundice, (see CONTRAINDICATIONS), increases in serum transaminases (AST and/or ALT), serum bilirubin, and/or alkaline phosphatase, has been infrequently reported with AUGMENTIN or AUGMENTIN XR. It has been reported more commonly in the elderly, in males, or in patients on prolonged treatment. The histologic findings on liver biopsy have consisted of predominantly cholestatic, hepatocellular, or mixed cholestatic-hepatocellular changes. The onset of signs/symptoms of hepatic dysfunction may occur during or several weeks after therapy has been discontinued. The hepatic dysfunction, which may be severe, is usually reversible. On rare occasions, deaths have been reported (less than 1 death reported per estimated 4 million prescriptions worldwide). These have generally been cases associated with serious underlying diseases or concomitant medications.

Renal

Interstitial nephritis and hematuria have been reported rarely. Crystalluria has also been reported (see OVERDOSAGE).

Hemic and Lymphatic Systems

Anemia, including hemolytic anemia, thrombocytopenia, thrombocytopenic purpura, eosinophilia, leukopenia, and agranulocytosis have been reported during therapy with penicillins. These reactions are usually reversible on discontinuation of therapy and are believed to be hypersensitivity phenomena. There have been reports of increased prothrombin time in patients receiving AUGMENTIN and anticoagulant therapy concomitantly.

Central Nervous System

Agitation, anxiety, behavioral changes, confusion, convulsions, dizziness, headache, insomnia, and reversible hyperactivity have been reported rarely.

Miscellaneous

Tooth discoloration (brown, yellow, or gray staining) has been rarely reported. Most reports occurred in pediatric patients. Discoloration was reduced or eliminated with brushing or dental cleaning in most cases.

OVERDOSAGE

Following overdosage, patients have experienced primarily gastrointestinal symptoms including stomach and abdominal pain, vomiting, and diarrhea. Rash, hyperactivity, or drowsiness have also been observed in a small number of patients.

In the case of overdosage, discontinue AUGMENTIN XR, treat symptomatically, and institute supportive measures as required. If the overdosage is very recent and there is no contraindication, an attempt at emesis or other means of removal of drug from the stomach may be performed. A prospective study of 51 pediatric patients at a poison control center suggested that overdosages of less than 250 mg/kg of amoxicillin are not associated with significant clinical symptoms and do not require gastric emptying.^5

Interstitial nephritis resulting in oliguric renal failure has been reported in a small number of patients after overdosage with amoxicillin.

Crystalluria, in some cases leading to renal failure, has also been reported after amoxicillin overdosage in adult and pediatric patients. In case of overdosage, adequate fluid intake and diuresis should be maintained to reduce the risk of amoxicillin crystalluria.

Renal impairment appears to be reversible with cessation of drug administration. High blood levels may occur more readily in patients with impaired renal function because of decreased renal clearance of both amoxicillin and clavulanate. Both amoxicillin and clavulanate are removed from the circulation by hemodialysis (see DOSAGE AND ADMINISTRATION).

DOSAGE AND ADMINISTRATION

AUGMENTIN XR should be taken at the start of a meal to enhance the absorption of amoxicillin and to minimize the potential for gastrointestinal intolerance. Absorption of the amoxicillin component is decreased when AUGMENTIN XR is taken on an empty stomach (see CLINICAL PHARMACOLOGY).

The recommended dose of AUGMENTIN XR is 4,000 mg/250 mg daily according to the following table:

Indication | Dose | Duration
Acute bacterial sinusitis | 2 tablets q12h | 10 days
Community-acquired pneumonia | 2 tablets q12h | 7-10 days

Tablets of AUGMENTIN (250 mg or 500 mg) CANNOT be used to provide the same dosages as AUGMENTIN XR Extended Release Tablets. This is because AUGMENTIN XR contains 62.5 mg of clavulanic acid, while the AUGMENTIN 250-mg and 500-mg tablets each contain 125 mg of clavulanic acid. In addition, the Extended Release Tablet provides an extended time course of plasma amoxicillin concentrations compared to immediate-release Tablets. Thus, two AUGMENTIN 500-mg tablets are not equivalent to one AUGMENTIN XR tablet.

Scored AUGMENTIN XR Extended Release Tablets are available for greater convenience for adult patients who have difficulty swallowing. The scored tablet is not intended to reduce the dosage of medication taken; as stated in the table above, the recommended dose of AUGMENTIN XR is two tablets twice a day (every 12 hours).

Renally Impaired Patients

The pharmacokinetics of AUGMENTIN XR have not been studied in patients with renal impairment. AUGMENTIN XR is contraindicated in patients with a creatinine clearance of < 30 mL/min. and in hemodialysis patients (see CONTRAINDICATIONS).

Hepatically Impaired Patients

Hepatically impaired patients should be dosed with caution and hepatic function monitored at regular intervals (see WARNINGS).

Pediatric Use

Pediatric patients who weigh 40 kg or more and can swallow tablets should receive the adult dose.

Geriatric Use

No dosage adjustment is required for the elderly (see PRECAUTIONS, Geriatric Use).

HOW SUPPLIED

AUGMENTIN XR Extended Release Tablets

Each white, oval film-coated bilayer scored tablet, debossed with AUGMENTIN XR, contains amoxicillin trihydrate and amoxicillin sodium equivalent to a total of 1,000 mg of amoxicillin and clavulanate potassium equivalent to 62.5 mg of clavulanic acid.

NDC 54868-4735-0 Bottles of 20

NDC 54868-4735-2 Bottles of 28 (7 day XR pack)

NDC 54868-4735-1 Bottles of 40 (10 day XR pack)

STORAGE

Store tablets at or below 25°C (77°F). Dispense in original container.

CLINICAL STUDIES

Acute Bacterial Sinusitis

Adults with a diagnosis of acute bacterial sinusitis (ABS) were evaluated in 3 clinical studies. In one study, 363 patients were randomized to receive either AUGMENTIN XR 2,000 mg/125 mg orally every 12 hours or levofloxacin 500 mg orally daily for 10 days in a double-blind, multicenter, prospective trial. These patients were clinically and radiologically evaluated at the test of cure (day 17-28) visit. The combined clinical and radiological responses were 83.7% for AUGMENTIN XR and 84.3% for levofloxacin at the test of cure visit in clinically evaluable patients (95% CI for the treatment difference = -9.4, 8.3). The clinical response rates at the test of cure were 87.0% and 88.6%, respectively.

The other 2 trials were non-comparative, multicenter studies designed to assess the bacteriological and clinical efficacy of AUGMENTIN XR (2,000 mg/125 mg orally every 12 hours for 10 days) in the treatment of 2288 patients with ABS. Evaluation timepoints were the same as in the prior study. Patients underwent maxillary sinus puncture for culture prior to receiving study medication. At test of cure, the clinical success rates were 87.5% and 86.6% (intention-to-treat) and 92.5% and 92.1% (per protocol populations).

Patients with acute bacterial sinusitis due to S. pneumoniae with reduced susceptibility to penicillin were accrued through enrollment in these 2 open-label non-comparative clinical trials. Microbiologic eradication rates for key pathogens in these studies are shown in the following table:

Clinical Outcome for ABS
Penicillin MICs of S. pneumoniae Isolates | Intent-To-Treat | Clinically Evaluable
n/Na | % | 95% CIb | n/Na | % | 95% CIb
All S. pneumoniae | 344/370 | 93.0 | — | 318/326 | 97.5 | —
MIC ≥ 2.0 mcg/mLc | 35/36 | 97.2 | 85.5, 99.9 | 30/31 | 95.8 | 83.3, 99.9
MIC = 2.0 mcg/mL | 23/24 | 95.8 | 78.9, 99.9 | 19/20 | 95.0 | 75.1, 99.9
MIC ≥ 4.0 mcg/mLd | 12/12 | 100 | 73.5, 100 | 11/11 | 100 | 71.5, 100
H. influenzae | 265/305 | 86.9 | — | 242/259 | 93.4 | —
M. catarrhalis | 94/105 | 89.5 | — | 86/90 | 95.6 | —

a n/N = patients with pathogen eradicated or presumed eradicated/total number of patients.

b Confidence limits calculated using exact probabilities.

c S. pneumoniae strains with penicillin MICs of ≥ 2 mcg/mL are considered resistant to penicillin.

d Includes one patient each with S. pneumoniae penicillin MICs of 8 and 16 mcg/mL.

Community-Acquired Pneumonia

Four randomized, controlled, double-blind clinical studies and one non-comparative study were conducted in adults with community-acquired pneumonia (CAP). In comparative studies, 904 patients received AUGMENTIN XR at a dose of 2,000 mg/125 mg orally every 12 hours for 7 or 10 days. In the non-comparative study to assess both clinical and bacteriological efficacy, 1,122 patients received AUGMENTIN XR 2,000 mg/125 mg orally every 12 hours for 7 days. In the 4 comparative studies, the combined clinical success rate at test of cure ranged from 86.3% to 94.7% in clinically evaluable patients who received AUGMENTIN XR; in the non-comparative study, the clinical success rate was 85.6%.

Data on the efficacy of AUGMENTIN XR in the treatment of community-acquired pneumonia due to S. pneumoniae with reduced susceptibility to penicillin were accrued from the 4 controlled clinical studies and the 1 non-comparative study. The majority of these cases were accrued from the non-comparative study.

Clinical Outcome for CAP due to S. pneumoniae
Penicillin MICs of S. pneumoniae Isolates | Intent-To-Treat | Clinically Evaluable
n/Na | % | 95% CIb | n/Na | % | 95% CIb
All S. pneumoniae | 318/367 | 86.6 | — | 275/297 | 92.6 | —
MIC ≥ 2.0 mcg/mLc | 30/35 | 85.7 | 69.7, 95.2 | 24/25 | 96.0 | 79.6, 99.9
MIC = 2.0 mcg/mL | 22/24 | 91.7 | 73.0, 99.0 | 18/18 | 100 | 81.5, 100
MIC ≥ 4.0 mcg/mLd | 8/11 | 72.7 | 39.0, 94.0 | 6/7 | 85.7 | 42.1, 99.6

a n/N = patients with pathogen eradicated or presumed eradicated/total number of patients.

b Confidence limits calculated using exact probabilities.

c S. pneumoniae strains with penicillin MICs of ≥ 2 mcg/mL are considered resistant to penicillin.

d Includes one patient each with S. pneumoniae penicillin MICs of 8 and 16 mcg/mL in the Intent-To-Treat group only.

Safety

In 2 randomized, double-blind, multicenter studies, AUGMENTIN XR (2,000 mg/125 mg orally every 12 hours, n = 577) was compared to AUGMENTIN (875 mg/125 mg orally every 12 hours, n = 570), administered for 7 days for the treatment of community-acquired pneumonia. Adverse events, regardless of relationship to test drug, were reported by 44.4% of patients who received AUGMENTIN XR (versus 46.3% in comparator group). Treatment-related adverse events were reported in 21.7% of patients who received AUGMENTIN XR (versus 21.2% in comparator group); most were mild and transient in nature. Adverse events which led to withdrawal were reported by 2.8% of patients who received AUGMENTIN XR (versus 5.3% in comparator group). In each group, the most frequently reported adverse events were diarrhea (14.4% versus 13.0%, p = 0.47), nausea (3.5 % versus 4.4%), and headache (3.5% versus 3.2%). Only 2 patients (0.3%) who received AUGMENTIN XR and 3 patients (0.5%) in the comparator group withdrew due to diarrhea. Serious adverse events considered suspected or probably related to test drug were reported in 0.3% of patients (versus 0.5% in comparator).

REFERENCES

1. Clinical and Laboratory Standards Institute (CLSI) (formerly the National Committee for Clinical Laboratory Standards). Performance Standards for Antimicrobial Susceptibility Testing − Twentieth Informational Supplement. CSLI Document M100-S20, Vol. 30, No. 1. CLSI, Wayne, PA, 2010.
2. Clinical and Laboratory Standards Institute (CLSI) (formerly the National Committee for Clinical Laboratory Standards). Methods for Antimicrobial Susceptibility Testing of Anaerobic Bacteria − Seventh Edition. Approved Standard CSLI Document M11-A7, Vol. 27, No. 2. CLSI, Wayne, PA, 2007.
3. Clinical and Laboratory Standards Institute (CLSI) (formerly the National Committee for Clinical Laboratory Standards). Methods for Dilution Antimicrobial Susceptibility Tests for Bacteria that Grow Aerobically − Eighth Edition. Approved Standard CLSI Document M7-A8, Vol. 29, No. 2. CLSI, Wayne, PA, 2009.
4. Clinical and Laboratory Standards Institute (CLSI) (formerly the National Committee for Clinical Laboratory Standards). Performance Standards for Antimicrobial Disk Susceptibility Tests − Tenth Edition. Approved Standard CLSI Document M2-A10, Vol. 29, No. 1. CLSI, Wayne, PA, 2009.
5. Swanson-Biearman B, Dean BS, Lopez G, Krenzelok EP. The effects of penicillin and cephalosporin ingestions in children less than six years of age. Vet Hum Toxicol 1988; 30: 66-67.

AUGMENTIN XR and AUGMENTIN are registered trademarks of GlaxoSmithKline.

MAALOX is a registered trademark of Novartis Consumer Health, Inc.

GlaxoSmithKline

Research Triangle Park, NC 27709

©2010, GlaxoSmithKline. All rights reserved.

September 2010 AUX:11PI

Relabeling and Repackaging by:
Physicians Total Care, Inc.
Tulsa, OK 74146

PRINCIPAL DISPLAY PANEL

AUGMENTIN XRTM

amoxicillin / clavulanate potassium

Extended Release Tablets

1000 mg

AMOXICILLIN, 1000 MG

CLAVULANIC ACID, 62.5 MG,

as clavulanate potassium

Store at or below 25oC (77oF). Dispense in original container; advise patients to keep in closed container.

Each tablet contains 1000 mg amoxicillin and 62.5 mg clavulanic acid as clavulanate potassium.

See prescribing information.

Use only if inner seal is intact.